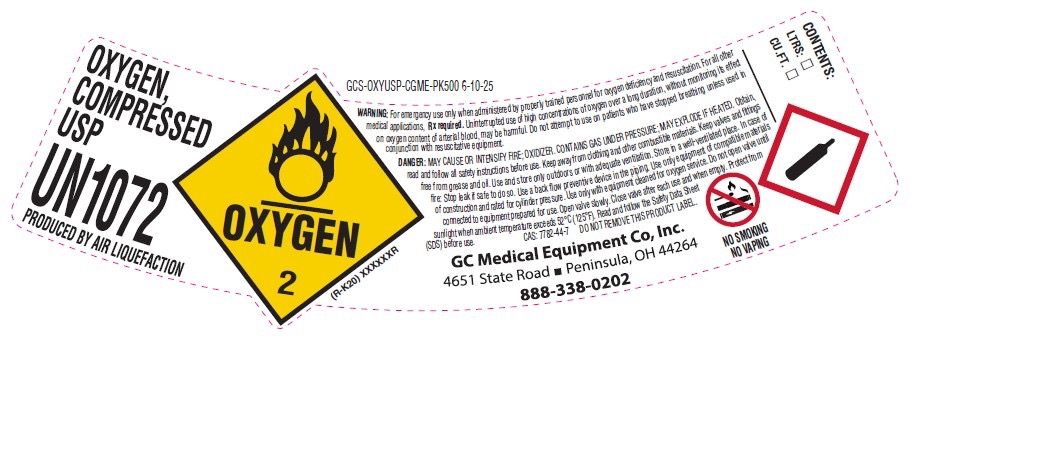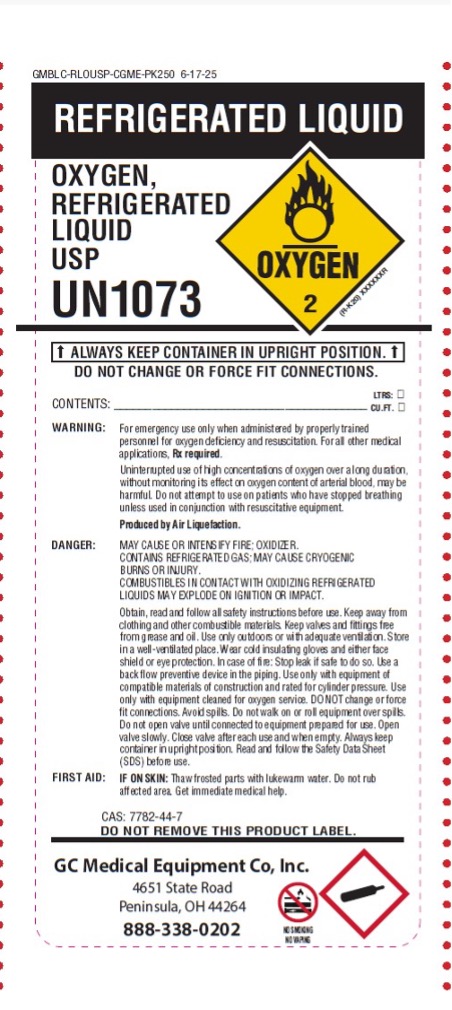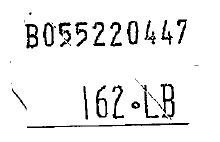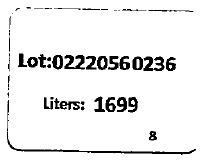 DRUG LABEL: Oxygen
NDC: 66878-001 | Form: GAS
Manufacturer: GC Medical Equipment, Inc.
Category: prescription | Type: HUMAN PRESCRIPTION DRUG LABEL
Date: 20251006

ACTIVE INGREDIENTS: OXYGEN 991 mL/1 L

Oxygen

PACKAGE LABEL

OXYGEN, COMPRESSED USP

UN1072

PRODUCED BY AIR LIQUEFACTION

WARNING:

For emergency use only when administered by properly trained personnel for oxygen deficiency and resuscitation. For all other medical applications, RX required. Uninterrupted use of high concentrations of oxygen over a long duration, without monitoring its effect on oxygen content of arterial blood, may be harmful. Do not attempt to use on patients who have stopped breathing unless used in conjunction with resuscitative equipment.

DANGER:

MAY CAUSE OR INTENSIFY FIRE; OXIDIZER. CONTAINS GAS UNDER PRESSURE; MAY EXPLODE IF HEATED. Obtain, read and follow all safety instructions before use. Keep away from clothing and other combustible materials. Keep valves and fittings free from grease and oil. Use only with equipment cleaned for oxygen service and rated for cylinder pressure. Use only with equipment of compatible materials of construction. Open valve slowly. Close valve after each use and when empty. Store and use with adequate ventilation. Protect from sunlight and physical damage. Always keep container in upright position. Use a backflow preventive device in the piping. Read and follow the Safety Data Sheet (SDS) before use.

CAS: 7782-44-7

DO NOT REMOVE THIS PRODUCT LABEL.

GC Medical Equipment Co., Inc.
4651 State Road
Peninsula, OH 44264
888-338-0202

NO SMOKING — NO VAPING

REFRIGERATED LIQUID

OXYGEN, REFRIGERATED LIQUID USP

UN1073

ALWAYS KEEP CONTAINER IN UPRIGHT POSITION.
DO NOT CHANGE OR FORCE FIT CONNECTIONS.

CONTENTS: _______ LTRS: _______ CU.FT.: _______

WARNING:

For emergency use only when administered by properly trained personnel for oxygen deficiency and resuscitation. For other medical applications, RX required.
Uninterrupted use of high concentrations of oxygen over a long duration, without monitoring its effect on oxygen content of arterial blood, may be harmful. Do not attempt to use on patients who have stopped breathing unless used in conjunction with resuscitative equipment.
Produced by Air Liquefaction.

DANGER:

MAY CAUSE OR INTENSIFY FIRE; OXIDIZER.
CONTAINS REFRIGERATED GAS; MAY CAUSE CRYOGENIC BURNS OR INJURY.
COMBUSTIBLES IN CONTACT WITH OXIDIZING REFRIGERATED LIQUID MAY EXPLODE ON IGNITION OR IMPACT.
Obtain, read and follow all safety instructions before use. Keep away from clothing and other combustible materials. Keep valves and fittings free from grease and oil. Use only outdoors or in well-ventilated area. Store and transport in upright position. Wear cold insulating gloves/face shield/eye protection. In case of fire: Stop leak if safe to do so. Use a backflow preventive device in the piping. Use only with equipment of compatible materials of construction and suitable for cryogenic service. Use only with equipment cleaned for oxygen service. DO NOT change or force fit connections. Avoid spills. Do not walk on or roll equipment over hoses. Close valve after each use and when empty. Always keep container in upright position. Read and follow the Safety Data Sheet (SDS) before use.

FIRST AID:

IF ON SKIN: Thaw frosted parts with lukewarm water. Do not rub affected area. Get immediate medical help.

CAS: 7782-44-7

DO NOT REMOVE THIS PRODUCT LABEL.

GC Medical Equipment Co., Inc.
4651 State Road
Peninsula, OH 44264
888-338-0202

NO SMOKING — NO VAPING